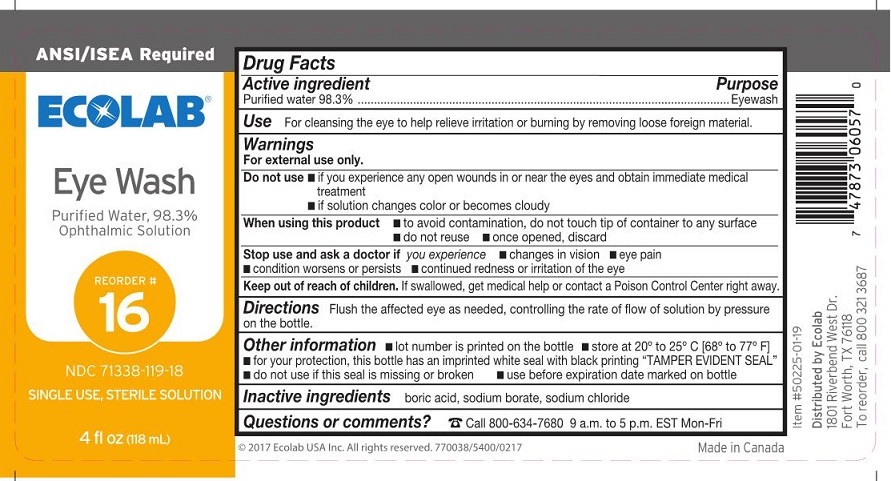 DRUG LABEL: ECOLAB Eye Wash
NDC: 71338-119 | Form: LIQUID
Manufacturer: ECOLAB Food Safety Specialties, Inc.
Category: otc | Type: HUMAN OTC DRUG LABEL
Date: 20250908

ACTIVE INGREDIENTS: WATER 0.983 mg/1 mL
INACTIVE INGREDIENTS: BORIC ACID; SODIUM BORATE; SODIUM CHLORIDE

ECOLAB Eye Wash

Drug Facts

Active ingredient

Purified water, 98.3%

Purpose

Eye wash

Use

For cleansing the eye to help releive irritation or burning by removing foreign material.

Warnings

For external use only.

Do not use

- if you experience any open wounds in or near the eyes and obtain immediate medical treatment
- if solution changes color or becomes cloudy

When using this product

- to avoid contamination, do not touch tip of container to any surface
- do not reuse
- once opened, discard

Stop use and ask a doctor if

you experience

- changes in vision
- eye pain
- condition worsens or persists
- continued redness or irritation of the eye

Keep out of reach of children.

If swallowed, get medical help or contact a apoison Control Center right away.

Directions

Flush affected eye as needed, controlling the rate of flow of solution by pressure on the bottle.

Other information

- lot number is printed on the bottle
- store at 20° to 25°C (68° to 77°F)
- for your protection, this bottle has an imprinted white seal with black printing "Tamper Evident Seal"
- do not use if this seal is missing or broken
- use before expoiration date marked on bottle

Inactive ingredients

boric acid, sodium borate, sodium chloride

Questions or comments?

1-800-634-7680

ECHOLAB Eye Wash Label

ECOLAB®

Eye Wash

Reorder #

16

NDC 71338-119-18

Single use, Sterile Solution

4 fl oz (118 mL)